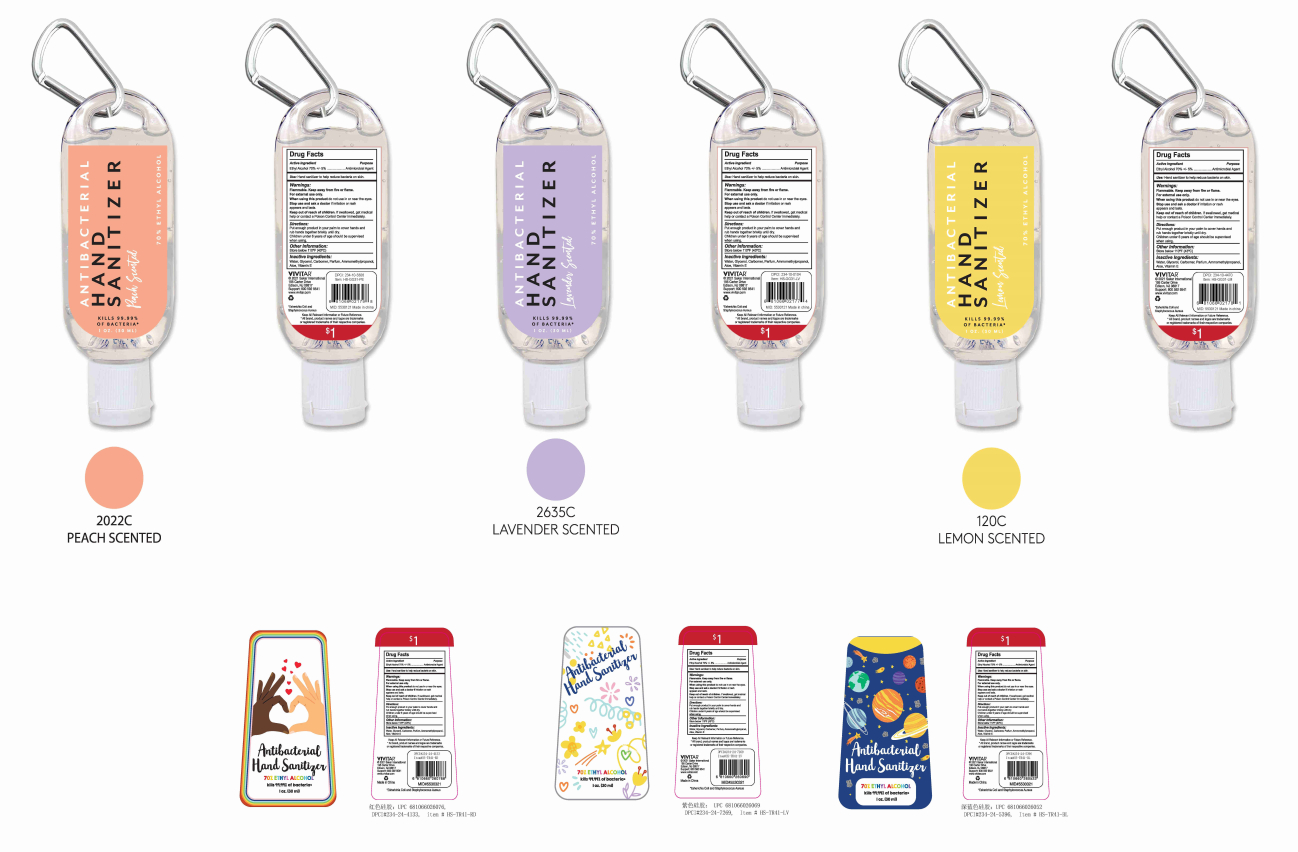 DRUG LABEL: Hand Sanitizer
NDC: 92863-006 | Form: GEL
Manufacturer: Yangzhou Huangxuan Daily Chemical Co., Ltd
Category: otc | Type: HUMAN OTC DRUG LABEL
Date: 20210225

ACTIVE INGREDIENTS: ALCOHOL 75 mL/100 mL
INACTIVE INGREDIENTS: WATER; TROLAMINE; GLYCERIN; CARBOMER HOMOPOLYMER, UNSPECIFIED TYPE

ACTIVE INGREDIENT

Ethyl Alcohol

PURPOSE

Antimicrobial Agent

Use

Hand sanitizer to help reduce bacteria on skin.

WARNINGS

Flammable. Keep away from fire or flame.

For external use only.
When using this product do not use in or near the eyes.

Stop use and ask a doctor if irritation or rash appears and lasts.
Keep out of reach of children. lf swallowed, get medicalhelp or contact a Poison Control Center immediately.

Directions

Put enough product in your palm to cover hands andrub hands together briskly until dry.
Children under 6 years of age should be supervised when using.

When using this product do not use in or near the eyes.

Stop use and ask a doctor if irritation or rash appears and lasts.

Keep out of reach of children. lf swallowed, get medicalhelp or contact a Poison Control Center immediately.

Other Information

Store below 110°F(43°C)

INACTIVE INGREDIENT

Water, Glycerol, Carbomer,Parfum, Ammomethylpropanol,Aloe, VitaminE